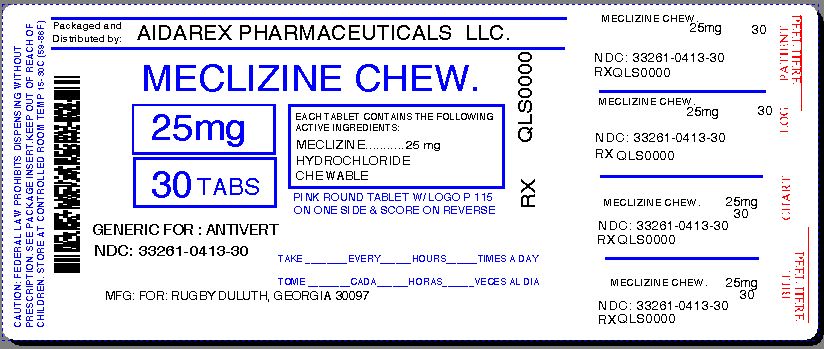 DRUG LABEL: Meclizine HCl
NDC: 33261-413 | Form: TABLET
Manufacturer: Aidarex Pharmaceuticals LLC
Category: otc | Type: HUMAN OTC DRUG LABEL
Date: 20140112

ACTIVE INGREDIENTS: MECLIZINE HYDROCHLORIDE 25 mg/1 1
INACTIVE INGREDIENTS: CROSCARMELLOSE SODIUM; ASPARTAME; MAGNESIUM STEARATE; CELLULOSE, MICROCRYSTALLINE; SUCROSE; DEXTROSE; FD&C RED NO. 40; RASPBERRY

Travel Sickness

Active Ingredient

(in each tablet)

Meclizine HCl 25 mg

Purpose

Antiemetic

Uses

prevents and treats nausea, vomiting, or dizziness due to motion sickness

WARNINGS

Ask a doctor before use if you have

- glaucoma
- a breathing problem such as emphysema or chronic bronchitis
- trouble urinating due to an enlarged prostate gland

Ask a doctor or pharmacist before use if you are taking sedatives or tranquilizers

When using this product

- you may get drowsy
- avoid alcoholic drinks
- alcohol, sedatives & tranquilizers may increase drowsiness
- be careful when driving a motor vehicle or operating machinery
  If pregnant or breast-feeding, ask a health professional before use.
  Keep out of reach of children. In case of overdose, get medical help or contact a Poison Control Center right away.

Directions

- take dose one hour before travel starts
- tablets can be chewed or swallowed whole with water
- adults & children 12 years and over: 1-2 tablets once daily
  children under 12 years: ask a doctor

Other Information

- phenylketonurics: each tablet contains: phenylalanine 0.28mg
- store at room temperature 15°-30°C (59°-86°F)

Inactive Ingredients

aspartame, compressible sugar, croscarmellose sodium, dextrose, FD&C red # 40(Al-lake), magnesium stearate, microcrystalline cellulose, raspberry flavor

Questions or Comments

Call 1-800-645-2158, 9 am – 5 pm ET, Monday - Friday

TAMPER EVIDENT: DO NOT USE IF IMPRINTED SAFETY SEAL UNDER CAP IS BROKEN OR MISSING

Rugby® Duluth, Georgia 30097

Repackaged By :
Aidarex Pharmaceuticals LLC,
Corona, CA 92880

PACKAGE LABEL.PRINCIPAL DISPLAY PANEL

Meclizine HCl

COMPARE TO ACTIVE INGREDIENT IN BONINE

Meclizine HCl 25 mg (ANTIEMETIC)

NDC 33261-0413-30

30 CHEWABLE TABLETS

Contains Aspartame

Rugby

Duluth, Georgia 30097

Repackaged By :
Aidarex Pharmaceuticals LLC,
Corona, CA 92880